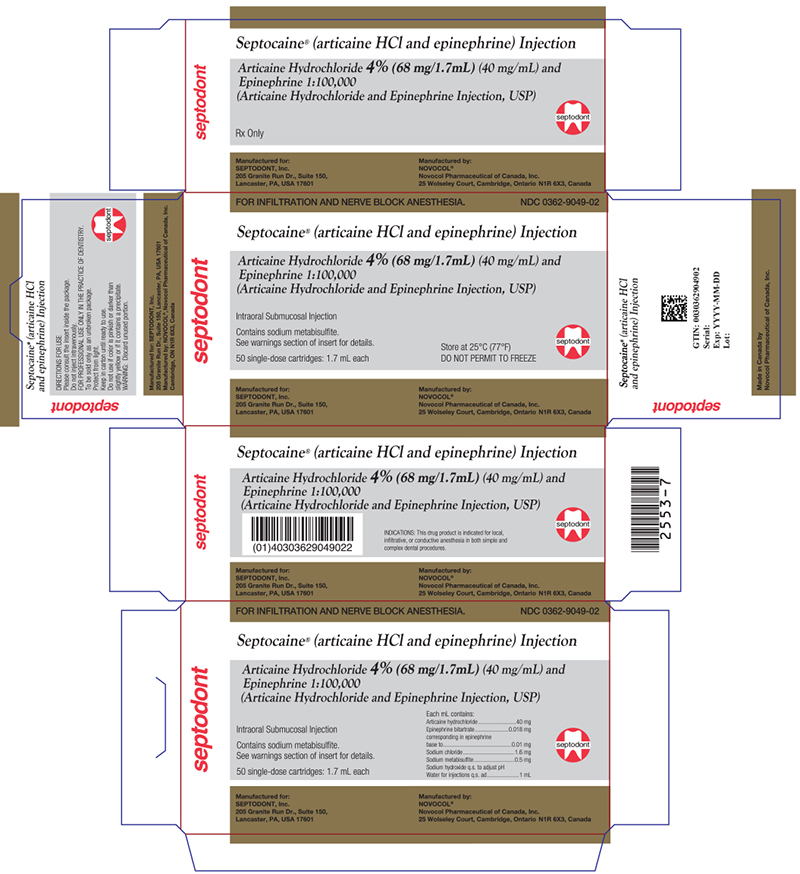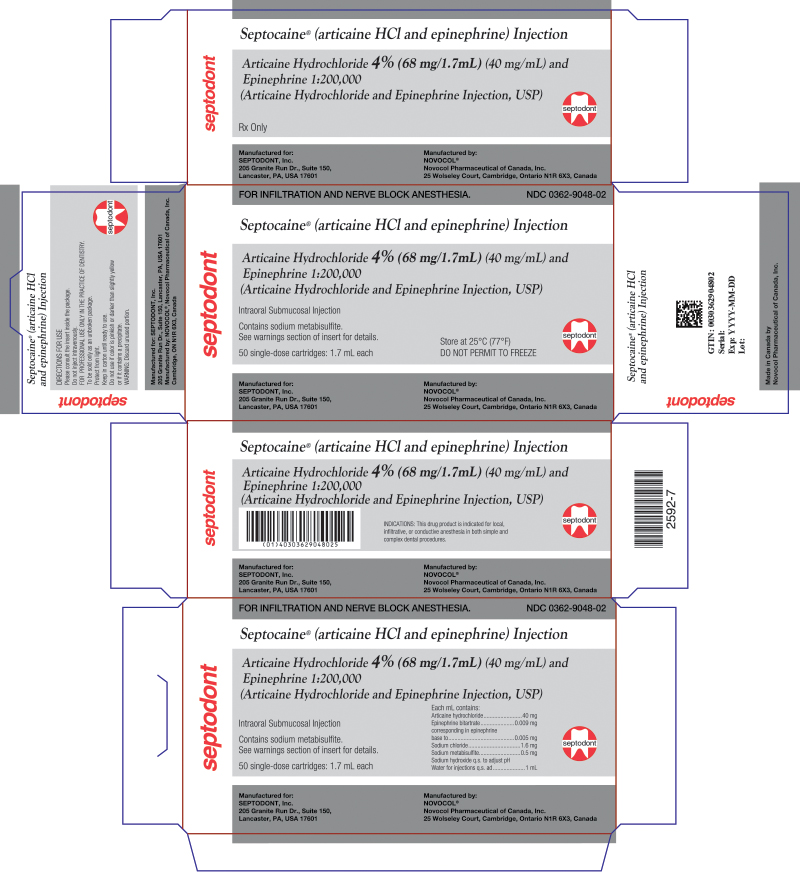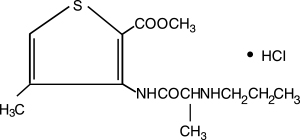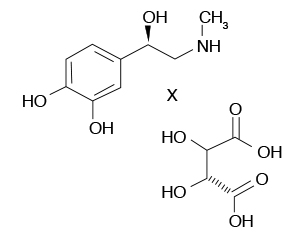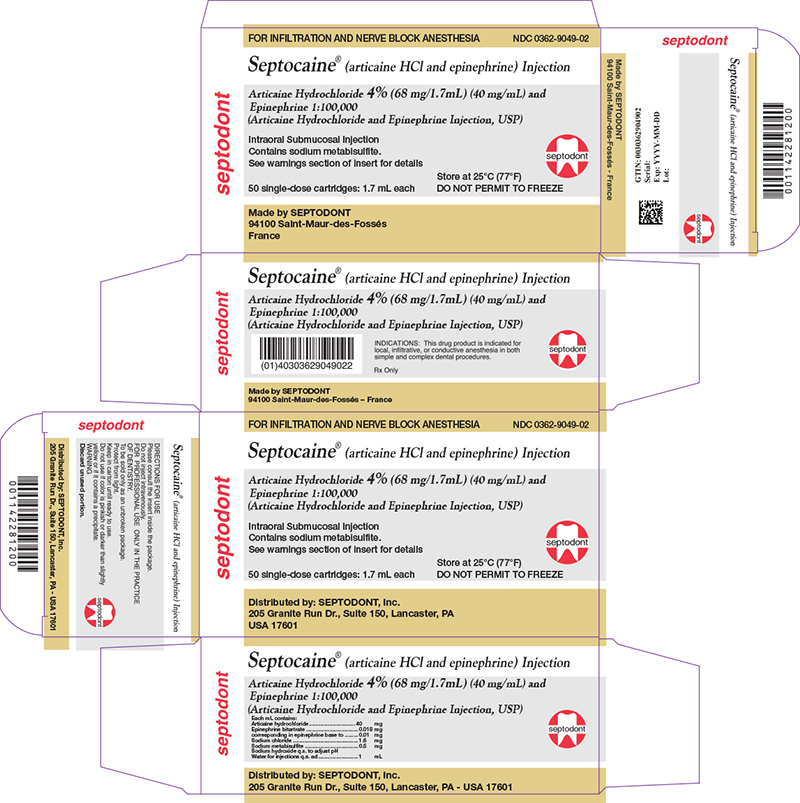 DRUG LABEL: Septocaine and Epinephrine
NDC: 0362-9049 | Form: INJECTION, SOLUTION
Manufacturer: Septodont Inc.
Category: prescription | Type: HUMAN PRESCRIPTION DRUG LABEL
Date: 20241023

ACTIVE INGREDIENTS: Articaine Hydrochloride 40 mg/1 mL; Epinephrine Bitartrate 0.01 mg/1 mL
INACTIVE INGREDIENTS: Sodium chloride 1.6 mg/1 mL; Sodium metabisulfite 0.5 mg/1 mL; Water; Sodium hydroxide

HIGHLIGHTS OF PRESCRIBING INFORMATION

These highlights do not include all the information needed to use SEPTOCAINE® safely and effectively. See full prescribing information for SEPTOCAINE®.
SEPTOCAINE® (articaine hydrochloride and epinephrine injection), for intraoral submucosal infiltration use
Initial U.S. Approval: 2000

RECENT MAJOR CHANGES

WARNINGS AND PRECAUTIONS, Methemoglobinemia (5.4)

1 INDICATIONS AND USAGE

SEPTOCAINE is a combination of articaine HCl, an amide local anesthetic, and epinephrine, a vasoconstrictor, indicated for local, infiltrative, or conductive anesthesia in both simple and complex dental procedures in adults and pediatric patients 4 years of age or older.

2 DOSAGE AND ADMINISTRATION

- For dental procedures by intraoral submucosal infiltration or nerve block. (2.1)

- For infiltration: 0.5-2.5 mL (20-100 mg articaine HCl)
- For nerve block: 0.5-3.4 mL (20-136 mg articaine HCl)
- For oral surgery: 1.0-5.1 mL (40-204 mg articaine HCl)

- For most routine dental procedures, SEPTOCAINE containing epinephrine 1:200,000 is preferred. However, when more pronounced hemostasis or improved visualization of the surgical field are required, SEPTOCAINE containing epinephrine 1:100,000 may be used. (2.1)

- Maximum recommended dosages (2.2):

- Healthy adults: 7 mg/kg of articaine HCl and 0.0017mg/kg of epineprhine (equivalent to 0.175 mL/kg for either product presentation,

articaine HCl and epinephrine 1:100,000 or 1:200,000)

- Pediatric patients 4-16 years: 7 mg/kg of articaine HCl and 0.0017mg/kg of epineprhine (equivalent to 0.175 mL/kg for either product

presentation, articaine HCl and epinephrine 1:100,000 or 1:200,000).

3 DOSAGE FORMS AND STRENGTHS

Injection provided in:

- Glass cartridges (single-dose) containing:

- Articaine hydrochloride 4% (68 mg/1.7mL) (40 mg/mL) and epineprhine 1:200,000 (as epinephrine bitartrate 0.009 mg/mL) (3)

- Articaine hydrochloride 4% (68 mg/1.7mL) (40 mg/mL) and epinephrine 1:100,000 (as epinephrine bitartrate 0.018 mg/mL) (3)

4 CONTRAINDICATIONS

Known hypersensitivity to sulfite. (4)

5 WARNINGS AND PRECAUTIONS

Accidental Intravascular Injection: May be associated with convulsions followed by coma and respiratory arrest. Resuscitative equipment, oxygen and other resuscitative drugs should be available. (5.1)

Systemic Toxicity: Systemic absorption of SEPTOCAINE can produce effects on the central nervous and cardiovascular systems. (5.2)

Vasoconstrictor Toxicity: Local anesthetic solutions like SEPTOCAINE that contain a vasoconstrictor should be used cautiously, especially in patients with impaired cardiovascular function or vascular disease. (5.3)

Methemoglobinemia: Cases of methemoglobinemia have been reported in association with local anesthetic use. (5.4)

6 ADVERSE REACTIONS

The most common adverse reactions (incidence >2%) are headache and pain. (6.1)

To report SUSPECTED ADVERSE REACTIONS, contact Septodont at 1-800-872-8305 or FDA at 1-800-FDA-1088 or www.fda.gov/medwatch.

7 DRUG INTERACTIONS

Monoamine Oxidase Inhibitors, Nonselective Beta-Adrenergic Antagonists, or Tricyclic Antidepressants: May produce severe, prolonged hypertension (7)

Phenothiazines and Butyrophenones: May reduce or reverse the pressor effect of epinephrine (7)

8 USE IN SPECIFIC POPULATIONS

Pregnancy: Based on animal studies, may cause fetal harm. (8.1)
Nursing Mothers: Exercise caution when administering to a nursing woman. (8.3)
Pediatric Use: Safety and effectiveness in pediatric patients below the age of 4 years have not been established. (8.4)

FULL PRESCRIBING INFORMATION

1 INDICATIONS AND USAGE

SEPTOCAINE is indicated for local, infiltrative, or conductive anesthesia in both simple and complex dental procedures in adults and pediatric patients 4 years of age or older.

2 DOSAGE AND ADMINISTRATION

2.1 Important Dosage Information

Table 1 summarizes the recommended dosages of SEPTOCAINE administered by intraoral submucosal infiltration or nerve block for various types of anesthetic dental procedures in healthy adults and pediatric patients.

Table 1: Recommended Dosages for Both Strengths
Procedure | Septocaine Injection
Procedure | Volume (mL) | Total dose of articaine HCl (mg)
Infiltration | 0.5 mL to 2.5 mL | 20 mg to 100 mg
Nerve block | 0.5 mL to 3.4 mL | 20 mg to 136 mg
Oral surgery | 1 mL to 5.1 mL | 40 mg to 204 mg

The recommended dosages of SEPTOCAINE in healthy adults serve only as a guide to the amount of anesthetic required for most routine dental procedures. The dosages to be used in adults depend on several factors such as type and extent of surgical procedure, depth of anesthesia, degree of muscular relaxation, and condition of the patient. In all cases, administer the lowest dosage that will produce the desired result.
The dosages of SEPTOCAINE to be used in pediatric patients aged 4 to 16 years old are determined by the age and weight of the patient and the type of dental procedure.
For most routine dental procedures, SEPTOCAINE containing epinephrine 1:200,000 is preferred. However, when more pronounced hemostasis or improved visualization of the surgical field are required, SEPTOCAINE containing epinephrine 1:100,000 may be used.
The onset of anesthesia and the duration of anesthesia are proportional to the dosage of the local anesthetic used. Exercise caution when employing large volumes because the incidence of adverse reactions may be dose-related.

2.2 Maximum Recommended Dosages

- Healthy Adults: The maximum recommended dosage of SEPTOCAINE is 7 mg/kg of articaine and 0.0017mg/kg of epinephrine (equivalent to 0.175 mL/kg for either product presentation, articaine HCl and 1:100,000 or 1:200,000 epinephrine).
- Pediatric Patients Ages 4 to 16 Years: The maximum recommended dosage of SEPTOCAINE is 7 mg/kg of articaine and 0.0017mg/kg of epinephrine (equivalent to 0.175 mL/kg for either product presentation, articaine HCl and 1:100,000 or 1:200,000 epinephrine) [see Use in Specific Populations (8.4)].

2.3 Dosage in Specific Populations

Lower dosages or dosage reduction may be required in debilitated patients, acutely ill patients, elderly patients, and pediatric patients commensurate with their age and physical condition. No studies have been performed in patients with renal or liver impairment. Exercise caution when using SEPTOCAINE in patients with severe liver disease. [see Warnings and Precautions (5.2), Use in Specific Populations (8.4, 8.5, and 8.6)]

2.4 Important Administration Instructions

Visually inspect SEPTOCAINE for particulate matter and discoloration prior to administration.
Prior to using the glass cartridges, disinfect by wiping the cap thoroughly with USP grade isopropyl alcohol (70%). Avoid use of isopropyl alcohol, as well as solutions of ethyl alcohol that are not of USP grade because they may contain denaturants that are injurious to rubber. Immersion is not recommended. Discard unused portion.

3 DOSAGE FORMS AND STRENGTHS

Injection (clear, colorless solution), provided in:

- Glass cartridges (single-dose) containing (less than a full cartridge or more than one cartridge may be used for an individual patient):

- Articaine hydrochloride 4% (68 mg/1.7mL) (40 mg/mL) and epinephrine 1:200,000 (as epinephrine bitartrate 0.009 mg/mL)
- Articaine hydrochloride 4% (68 mg/1.7mL) (40 mg/mL) and epinephrine 1:100,000 (as epinephrine bitartrate 0.018 mg/mL)

4 CONTRAINDICATIONS

SEPTOCAINE is contraindicated in patients who are hypersensitive to products containing sulfites. Products containing sulfites may cause allergic-type reactions including anaphylactic symptoms and life-threatening or less severe asthmatic episodes in certain susceptible people. Sulfite sensitivity is seen more frequently in asthmatic than in non-asthmatic people [see Warnings and Precautions (5.5)].

5 WARNINGS AND PRECAUTIONS

5.1 Accidental Intravascular Injection

Accidental intravascular injection of SEPTOCAINE may be associated with convulsions, followed by central nervous system or cardiorespiratory depression and coma, progressing ultimately to respiratory arrest. Dental practitioners who employ local anesthetic agents including SEPTOCAINE should be well versed in diagnosis and management of emergencies that may arise from their use. Resuscitative equipment, oxygen, and other resuscitative drugs should be available for immediate use. To avoid intravascular injection, aspiration should be performed before SEPTOCAINE is injected. The needle must be repositioned until no return of blood can be elicited by aspiration. Note, however, that the absence of blood in the syringe does not guarantee that intravascular injection has been avoided.

Small doses of local anesthetics injected in dental blocks may produce adverse reactions similar to systemic toxicity seen with unintentional intravascular injections of larger doses. Confusion, convulsions, respiratory depression or respiratory arrest, and cardiovascular stimulation or depression have been reported. These reactions may be due to intra-arterial injection of the local anesthetic with retrograde flow to the cerebral circulation. Patients receiving these blocks should be observed constantly. Resuscitative equipment and personnel for treating adverse reactions should be immediately available. Dosage recommendations should not be exceeded [see Dosage and Administration (2.1)].

5.2 Systemic Toxicity

This includes toxicity arising from accidental intravascular injection of SEPTOCAINE discussed in Section 5.1, as well as that related to higher systemic concentrations of local anesthetics or epinephrine [see Warnings and Precautions (5.3)]. Systemic absorption of local anesthetics including SEPTOCAINE can produce effects on the central nervous and cardiovascular systems.

At blood concentrations achieved with therapeutic doses of SEPTOCAINE, changes in cardiac conduction, excitability, refractoriness, contractility, and peripheral vascular resistance are minimal. However, toxic blood concentrations of SEPTOCAINE can depress cardiac conduction and excitability, which may lead to atrioventricular block, ventricular arrhythmias, and cardiac arrest, possibly resulting in fatalities. In addition, myocardial contractility is depressed and peripheral vasodilatation occurs, leading to decreased cardiac output and arterial blood pressure. SEPTOCAINE should also be used with caution in patients with heart block as well as those with impaired cardiovascular function since they may be less able to compensate for functional changes associated with the prolongation of A-V conduction produced by these drugs.

Restlessness, anxiety, tinnitus, dizziness, blurred vision, tremors, depression, or drowsiness may be early warning signs of central nervous system toxicity.

Careful and constant monitoring of cardiovascular and respiratory (adequacy of ventilation) vital signs and the patient's state of consciousness should be performed after each local anesthetic injection of SEPTOCAINE. Repeated doses of SEPTOCAINE may cause significant increases in blood levels because of possible accumulation of the drug or its metabolites. The lowest dosage that results in effective anesthesia should be used to decrease the risk of high plasma levels and serious adverse effects. Tolerance to elevated blood levels varies with the status of the patient. Resuscitative equipment, oxygen, and other resuscitative drugs should be available for immediate use. Precautions for epinephrine administration, discussed in Section 5.3, should be observed.

Debilitated patients, elderly patients, acutely ill patients, and pediatric patients should be given reduced doses commensurate with their age and physical condition [see Dosage and Administration (2.1, 2.3)]. No studies have been performed in patients with liver impairment, and caution should be used in patients with severe hepatic disease.

5.3 Vasoconstrictor Toxicity

SEPTOCAINE contains epinephrine, a vasoconstrictor that can cause local or systemic toxicity and should be used cautiously. Local toxicity may include ischemic injury or necrosis, which may be related to vascular spasm. SEPTOCAINE should be used with caution in patients during and following the administration of potent general anesthetic agents, since cardiac arrhythmias may occur under such conditions. Patients with peripheral vascular disease and those with hypertensive vascular disease may exhibit exaggerated vasoconstrictor response.

The American Heart Association has made the following recommendation regarding the use of local anesthetics with vasoconstrictors in patients with ischemic heart disease: "Vasoconstrictor agents should be used in local anesthesia solutions during dental practice only when it is clear that the procedure will be shortened or the analgesia rendered more profound. When a vasoconstrictor is indicated, extreme care should be taken to avoid intravascular injection. The minimum possible amount of vasoconstrictor should be used." (Kaplan, 1986).

It is essential to aspirate before any injection to avoid administration of the drug into the blood stream.

5.4 Methemoglobinemia

Cases of methemoglobinemia have been reported in association with local anesthetic use. Although all patients are at risk for methemoglobinemia, patients with glucose-6-phosphate dehydrogenase deficiency, congenital or idiopathic methemoglobinemia, cardiac or pulmonary compromise, infants under 6 months of age, and concurrent exposure to oxidizing agents or their metabolites are more susceptible to
developing clinical manifestations of the condition. If local anesthetics must be used in these patients, close monitoring for symptoms and signs of methemoglobinemia is recommended.
Signs of methemoglobinemia may occur immediately or may be delayed some hours after exposure and are characterized by a cyanotic skin discoloration, and/or abnormal coloration of the blood. Methemoglobin levels may continue to rise; therefore, immediate treatment is required to avert more serious central nervous system and cardiovascular adverse effects, including seizures, coma, arrhythmias, and death. Discontinue SEPTOCAINE and any other oxidizing agents. Depending on the severity of the signs and symptoms, patients may respond to supportive care, i.e., oxygen therapy, hydration. A more severe clinical presentation may require treatment with methylene blue, exchange transfusion, or hyperbaric oxygen.

5.5 Anaphylaxis and Allergic-Type Reactions

SEPTOCAINE contains sodium metabisulfite, a sulfite that may cause allergic-type reactions including anaphylactic symptoms and life-threatening or less severe asthmatic episodes in certain susceptible people. The overall prevalence of sulfite sensitivity in the general population is unknown. Sulfite sensitivity is seen more frequently in asthmatic than in non-asthmatic people.

6 ADVERSE REACTIONS

Reactions to articaine are characteristic of those associated with other amide-type local anesthetics. Adverse reactions to this group of drugs may also result from excessive plasma levels (which may be due to overdosage, unintentional intravascular injection, or slow metabolic degradation), injection technique, volume of injection, or hypersensitivity or they may be idiosyncratic.

6.1 Clinical Studies Experience

Because clinical trials are conducted under widely varying conditions, adverse reaction rates observed in the clinical trials of a drug cannot be directly compared to rates in the clinical trials of another drug and may not reflect the rates observed in practice.

The reported adverse reactions are derived from clinical trials in the United States and the United Kingdom. Table 2 displays the adverse reactions reported in clinical trials where 882 individuals were exposed to SEPTOCAINE containing epinephrine 1:100,000. Table 3 displays the adverse reactions reported in clinical trials where 182 individuals were exposed to SEPTOCAINE containing epinephrine 1:100,000 and 179 individuals were exposed to SEPTOCAINE containing epinephrine 1:200,000.

Adverse reactions observed in at least 1% of patients:

Table 2: Adverse Reactions in Controlled Trials with an Incidence of 1% or Greater in Patients Administered SEPTOCAINE containing Epinephrine 1:100,000
Body System/Reaction | SEPTOCAINE containing epinephrine 1:100,000 (N=882) Incidence
Body as a whole
Face Edema | 13 (1%)
Headache | 31 (4%)
Infection | 10 (1%)
Pain | 114 (13%)
Digestive system
Gingivitis | 13 (1%)
Nervous system
Paresthesia | 11 (1%)

Table 3: Adverse Reactions in Controlled Trials with an Incidence of 1% or Greater in Patients Administered Septocaine containing Epinephrine 1:200,000 and Septocaine containing Epinephrine 1:100,000
Reaction | SEPTOCAINE with epinephrine 1:200,000 (N=179) Incidence | SEPTOCAINE with epinephrine 1:100,000 (N=182) Incidence
Any adverse reaction | 33 (18%) | 35 (19%)
Pain | 11 (6.1%) | 14 (7.6%)
Headache | 9 (5%) | 6 (3.2%)
Positive blood aspiration into syringe | 3 (1.6%) | 6 (3.2%)
Swelling | 3 (1.6%) | 5 (2.7%)
Trismus | 1 (0.5%) | 3 (1.6%)
Nausea and emesis | 3 (1.6%) | 0 (0%)
Sleepiness | 2 (1.1%) | 1 (0.5%)
Numbness and tingling | 1 (0.5%) | 2 (1%)
Palpitation | 0 (0%) | 2 (1.%)
Ear symptoms (earache, otitis media) | 1 (0.5%) | 2 (1%)
Cough, persistent cough | 0 (0%) | 2 (1%)

Adverse reactions observed in less than 1% of patients:

Table 4: Adverse Reactions in Controlled Trials with an Incidence of Less than 1% but Considered Clinically Relevant in Patients Administered SEPTOCAINE
Body System | Reactions
Body as a Whole | Asthenia; back pain; injection site pain; burning sensation above injection site; malaise; neck pain
Cardiovascular System | Hemorrhage; migraine; syncope; tachycardia; elevated blood pressure
Digestive System | Dyspepsia; glossitis; gum hemorrhage; mouth ulceration; nausea; stomatitis; tongue edemas; tooth disorder; vomiting
Hemic and Lymphatic System | Ecchymosis; lymphadenopathy
Metabolic and Nutritional System | Edema; thirst
Musculoskeletal System | Arthralgia; myalgia; osteomyelitis
Nervous System | Dizziness; dry mouth; facial paralysis; hyperesthesia; increased salivation; nervousness; neuropathy; paresthesia; somnolence; exacerbation of Kearns-Sayre Syndrome
Respiratory System | Pharyngitis; rhinitis; sinus pain; sinus congestion
Skin and Appendages | Pruritus; skin disorder
Special Senses | Ear pain; taste perversion

6.2 Postmarketing Experience

The following adverse reactions have been identified during postapproval use of SEPTOCAINE. Because these reactions are reported voluntarily from a population of uncertain size, it is not always possible to reliably estimate their frequency or establish a casual relationship to drug exposure.

Persistent paresthesias of the lips, tongue, and oral tissues have been reported with use of articaine hydrochloride, with slow, incomplete, or no recovery. These postmarketing events have been reported chiefly following nerve blocks in the mandible and have involved the trigeminal nerve and its branches.

Hypoesthesia has been reported with use of articaine, especially in pediatric age groups, which is usually reversible. Prolonged numbness can result in soft tissue injuries such as that of the lips and tongue in these age groups.

Ischemic injury and necrosis have been described following use of articaine with epinephrine and have been postulated to be due to vascular spasm of terminal arterial branches.

Paralysis of ocular muscles has been reported, especially after posterior, superior alveolar injections of articaine during dental anesthesia. Symptoms include diplopia, mydriasis, ptosis, and difficulty in abduction of the affected eye. These symptoms have been described as developing immediately after injection of the anesthetic solution and persisting one minute to several hours, with generally complete recovery.

7 DRUG INTERACTIONS

The administration of local anesthetic solutions containing epinephrine to patients receiving monoamine oxidase inhibitors, nonselective beta-adrenergic antagonists, or tricyclic antidepressants may produce severe, prolonged hypertension. Phenothiazines and butyrophenones may reduce or reverse the pressor effect of epinephrine. Concurrent use of these agents should be avoided; however, in situations when concurrent therapy is necessary, careful patient monitoring is essential [see Warnings and Precautions (5.2)]. Patients who are administered local anesthetics are at increased risk of developing methemoglobinemia when concurrently exposed to the following drugs, which could include other local anesthetics:

Table 5. Examples of Drugs Associated with Methemoglobinemia:
Class | Examples
Nitrates/Nitrites | nitric oxide, nitroglycerin, nitroprusside, nitrous oxide
Local anesthetics | articaine, benzocaine, bupivacaine, lidocaine, mepivacaine, prilocaine, procaine, ropivacaine, tetracaine
Antineoplastic agents | cyclophosphamide, flutamide, hydroxyurea, ifosfamide, rasburicase
Antibiotics | dapsone, nitrofurantoin, para-aminosalicylic acid, sulfonamides
Antimalarials | chloroquine, primaquine
Anticonvulsants | phenobarbital, phenytoin, sodium valproate
Other drugs | acetaminophen, metoclopramide, quinine, sulfasalazine

8 USE IN SPECIFIC POPULATIONS

8.1 Pregnancy

Teratogenic Effects - Pregnancy Category C.

There are no adequate and well-controlled studies in pregnant women with SEPTOCAINE. Articaine hydrochloride and epinephrine (1:100,000) has been shown to increase fetal deaths and skeletal variations in rabbits when given in doses approximately 4 times the maximum recommended human dose (MRHD). SEPTOCAINE should be used during pregnancy only if the potential benefit justifies the potential risk to the fetus.

In embryo-fetal toxicity studies in rabbits, 80 mg/kg, subcutaneously (approximately 4 times the MRHD based on body surface area) caused fetal death and increased fetal skeletal variations, but these effects may be attributable to severe maternal toxicity, including seizures, observed at this dose. In contrast, no embryo-fetal toxicities were observed when articaine and epinephrine (1:100,000) was administered subcutaneously throughout organogenesis at doses up to 40 mg/kg in rabbits and 80 mg/kg in rats (approximately 2 times the MRHD based on body surface area).

In pre- and postnatal developmental studies subcutaneous administration of articaine hydrochloride to pregnant rats throughout gestation and lactation, at a dose of 80 mg/kg (approximately 2 times the MRHD based on body surface area) increased the number of stillbirths and adversely affected passive avoidance, a measure of learning, in pups. This dose also produced severe maternal toxicity in some animals. A dose of 40 mg/kg (approximately equal to the MRHD on a mg/m^2 basis) did not produce these effects. A similar study using articaine and epinephrine (1:100,000) rather than articaine hydrochloride alone produced maternal toxicity, but no effects on offspring.

8.3 Nursing Mothers

It is not known whether SEPTOCAINE is excreted in human milk. Because many drugs are excreted in human milk, caution should be exercised when SEPTOCAINE is administered to a nursing woman. When using SEPTOCAINE, nursing mothers may choose to pump and discard breast milk for approximately 4 hours (based on plasma half life) following an injection of SEPTOCAINE (to minimize infant ingestion) and then resume breastfeeding.

8.4 Pediatric Use

Safety and effectiveness of SEPTOCAINE in pediatric patients below the age of 4 years have not been established. Safety of doses greater than 7 mg/kg (0.175 mL/kg) in pediatric patients has not been established.
The safety and effectiveness of SEPTOCAINE for local, infiltrative, or conductive anesthesia in both simple and complex dental procedures have been established in pediatric patients ages 4 to 16 years old. Safety and effectiveness was established in clinical trials with 61 pediatric patients between the ages of 4 and 16 years administered articaine hydrochloride 4% and epinephrine 1:100,000 injections. Fifty-one of these patients received doses from 0.76 mg/kg to 5.65 mg/kg (0.9 to 5.1 mL) for simple dental procedures and 10 patients received doses between 0.37 mg/kg and 7.48 mg/kg (0.7 to 3.9 mL) for complex dental procedures. Approximately 13% of these pediatric patients required additional injections of anesthetic for complete anesthesia. Dosages in pediatric patients should be reduced, commensurate with age, body weight, and physical condition [see Dosage and Administration (2.2)].

8.5 Geriatric Use

In clinical trials, 54 patients between the ages of 65 and 75 years, and 11 patients 75 years and over received SEPTOCAINE containing epinephrine 1:100,000. Among all patients between 65 and 75 years, doses from 0.43 mg/kg to 4.76 mg/kg (0.9 to 11.9 mL) were administered to 35 patients for simple procedures and doses from 1.05 mg/kg to 4.27 mg/kg (1.3 to 6.8 mL) were administered to 19 patients for complex procedures. Among the 11 patients ≥ 75 years old, doses from 0.78 mg/kg to 4.76 mg/kg (1.3 to 11.9 mL) were administered to 7 patients for simple procedures and doses of 1.12 mg/kg to 2.17 mg/kg (1.3 to 5.1 mL) were administered to 4 patients for complex procedures.

Approximately 6% of patients between the ages of 65 and 75 years and none of the 11 patients 75 years of age or older required additional injections of anesthetic for complete anesthesia compared with 11% of patients between 17 and 65 years old who required additional injections.

No overall differences in safety or effectiveness were observed between elderly subjects and younger subjects, and other reported clinical experience has not identified differences in responses between the elderly and younger patients, but greater sensitivity of some older individuals cannot be ruled out.

8.6 Renal/Hepatic Impairment

No studies have been performed with articaine hydrochloride 4% and epinephrine 1:200,000 injection or articaine hydrochloride 4% and epinephrine 1:100,000 injection in patients with renal or hepatic impairment [see Warnings and Precautions (5.2)].

10 OVERDOSAGE

Acute emergencies from local anesthetics are generally related to high plasma levels encountered during therapeutic use of local anesthetics or to unintended subarachnoid injection of local anesthetic solution [see Warnings and Precautions (5.1, 5.2)].

The first consideration is prevention, best accomplished by careful and constant monitoring of cardiovascular and respiratory vital signs and the patient's state of consciousness after each local anesthetic injection. At the first sign of change, oxygen should be administered.

The first step in the management of convulsions, as well as hypo-ventilation, consists of immediate attention to the maintenance of a patent airway and assisted or controlled ventilation as needed. The adequacy of the circulation should be assessed. Should convulsions persist despite adequate respiratory support, treatment with appropriate anticonvulsant therapy is indicated. The practitioner should be familiar with the use of anticonvulsant drugs, prior to the use of local anesthetics. Supportive treatment of circulatory depression may require administration of intravenous fluids and, when appropriate, a vasopressor.

If not treated immediately, both convulsions and cardiovascular depression can result in hypoxia, acidosis, bradycardia, arrhythmias, and/or cardiac arrest. If cardiac arrest should occur, standard cardiopulmonary resuscitative measures should be instituted.

For additional information about overdose treatment, call a poison control center (1-800-222-1222).

11 DESCRIPTION

SEPTOCAINE (articaine hydrochloride and epinephrine injection), for intraoral submucosal infiltration use, is a sterile, aqueous solution that contains articaine HCl 4% (68 mg/1.7mL) (40 mg/mL) and epinephrine bitartrate in an epinephrine 1:200,000 or epinephrine 1:100,000 strength.
Articaine HCl is an amino amide local anesthetic, chemically designated as 4-methyl-3-[2-(propylamino)-propionamido]-2-thiophene-carboxylic acid, methyl ester hydrochloride and is a racemic mixture.

Articaine HCl has a molecular weight of 320.84 and the following structural formula:

Articaine HCl has a partition coefficient in n-octanol/Soerensen buffer (pH 7.35) of 17 and a pKa of 7.8.

Epinephrine bitartrate, (-)-1-(3,4-Dihydroxyphenyl)-2-methylamino-ethanol (+) tartrate (1:1) salt, is a vasoconstrictor with a concentration of 1:200,000 or 1:100,000 (expressed as free base). It has a molecular weight of 333.3 and the following structural formula:

SEPTOCAINE contains the following inactive ingredients: sodium chloride (1.6 mg/mL) and sodium metabisulfite (0.5 mg/mL). The product is formulated with a 15% overage of epinephrine. The pH is adjusted with sodium hydroxide.

12 CLINICAL PHARMACOLOGY

12.1 Mechanism of Action

Articaine HCl is an amide local anesthetic. Local anesthetics block the generation and conduction of nerve impulses, presumably by increasing the threshold for electrical excitation in the nerve, by slowing the propagation of the nerve impulse, and by reducing the rate of rise of the action potential. In general, the progression of anesthesia is related to the diameter, myelination, and conduction velocity of the affected nerve fibers. Epinephrine is a vasoconstrictor added to articaine HCl to slow absorption into the general circulation and thus prolong maintenance of an active tissue concentration.

12.2 Pharmacodynamics

Clinically, the order of loss of nerve function is as follows: (1) pain; (2) temperature; (3) touch; (4) proprioception; and (5) skeletal muscle tone.

The onset of anesthesia has been shown to be within 1 to 9 minutes of injection of SEPTOCAINE. Complete anesthesia lasts approximately 1 hour for infiltrations and up to approximately 2 hours for nerve block.

Administration of SEPTOCAINE results in a 3- to 5-fold increase in plasma epinephrine concentrations compared to baseline; however, in healthy adults it does not appear to be associated with marked increases in blood pressure or heart rate, except in the case of accidental intravascular injection [see Warnings and Precautions (5.1)].

12.3 Pharmacokinetics

Absorption

Following dental injection by the submucosal route of an articaine solution containing epinephrine 1:200,000, articaine reaches peak blood concentration about 25 minutes after a single dose injection and 48 minutes after three doses. Peak plasma levels of articaine achieved after 68 and 204 mg doses are 385 and 900 ng/mL, respectively. Following intraoral administration of a near maximum dose of 476 mg, articaine reaches peak blood concentrations of 2037 and 2145 ng/mL for articaine solution containing epinephrine 1:100,000 and 1:200,000, respectively, approximately 22 minutes post-dose.

Distribution

Approximately 60 to 80% of articaine HCl is bound to human serum albumin and γ-globulins at 37°C in vitro.

Elimination

Metabolism: Articaine HCl is metabolized by plasma carboxyesterase to its primary metabolite, articainic acid, which is inactive. In vitro studies show that the human liver microsome P450 isoenzyme system metabolizes approximately 5% to 10% of available articaine with nearly quantitative conversion to articainic acid.

Excretion: At the dose of 476 mg of articaine, the elimination half-life was 43.8 minutes and 44.4 minutes for articaine solution containing epinephrine 1:100,000 and 1:200,000, respectively. Articaine is excreted primarily through urine with 53-57% of the administered dose eliminated in the first 24 hours following submucosal administration. Articainic acid is the primary metabolite in urine. A minor metabolite, articainic acid glucuronide, is also excreted in urine. Articaine constitutes only 2% of the total dose excreted in urine.

13 NONCLINICAL TOXICOLOGY

13.1 Carcinogenesis, Mutagenesis, Impairment of Fertility

Studies to evaluate the carcinogenic potential of articaine HCl in animals have not been conducted. Five standard mutagenicity tests, including three in vitro tests (the nonmammalian Ames test, the mammalian Chinese hamster ovary chromosomal aberration test, and a mammalian gene mutation test with articaine HCl) and two in vivo mouse micronucleus tests (one with articaine and epinephrine 1:100,000 and one with articaine HCl alone) showed no mutagenic effects.

No effects on male or female fertility were observed in rats for articaine and epinephrine 1:100,000 administered subcutaneously in doses up to 80 mg/kg/day (approximately 2 times the MRHD based on body surface area).

14 CLINICAL STUDIES

Three randomized, double-blind, active-controlled studies were designed to evaluate effectiveness of SEPTOCAINE containing epinephrine 1:100,000 as a dental anesthetic. Patients ranging in age from 4 years to over 65 years old underwent simple dental procedures such as single uncomplicated extractions, routine operative procedures, single apical resections, and single crown procedures, or complex dental procedures such as multiple extractions, multiple crowns and/or bridge procedures, multiple apical resections, alveolectomies, muco-gingival operations, and other surgical procedures on the bone. SEPTOCAINE containing epinephrine 1:100,000 was administered by intraoral submucosal infiltration or nerve block for these dental procedures.

Efficacy was measured immediately following the procedure by having the patient and investigator rate the patient's procedural pain using a 10 cm visual analog scale (VAS), in which a score of zero represented no pain and a score of 10 represented the worst pain imaginable. Mean patient and investigator VAS pain scores were 0.3-0.4 cm for simple procedures and 0.5-0.6 cm for complex procedures.

Four randomized, double-blind, active-controlled studies were performed comparing SEPTOCAINE containing epinephrine 1:100,000 versus SEPTOCAINE containing epinephrine 1:200,000. The first two studies used electric pulp testers (EPT) to evaluate the success rate (maximum EPT value within 10 minutes), onset, and duration of SEPTOCAINE containing epinephrine 1:100,000 versus SEPTOCAINE containing epinephrine 1:200,000 and articaine solution without epinephrine in healthy adults between 18 and 65 years old. Results indicated that the anesthetic characteristics of the 1:100,000 and 1:200,000 formulations are not significantly different.

A third study compared the difference in visualization of the surgical field after administration of SEPTOCAINE containing epinephrine 1:100,000 versus SEPTOCAINE containing epinephrine 1:200,000 during bilateral maxillary periodontal surgeries in patients ranging from 21 to 65 years old. SEPTOCAINE containing epinephrine 1:100,000 provided better visualization of the surgical field and less blood loss during the procedures. In a fourth study, designed to assess and compare cardiovascular safety, when the maximum dose of each formulation was administered, no clinically relevant differences in blood pressure or heart rate between formulations were observed.

15 REFERENCES

Kaplan, EL, editor. Cardiovascular disease in dental practice. Dallas; American Heart Association; 1986.

16 HOW SUPPLIED/STORAGE AND HANDLING

SEPTOCAINE (articaine hydrochloride and epinephrine) injection is a clear, colorless solution available in 1.7 mL single-dose glass cartridges, packaged in boxes of 50 cartridges in the following two strengths (less than a full cartridge or more than one cartridge may be used for an individual patient):

- Articaine HCl 4% (68 mg/1.7mL) (40 mg/mL) and epinephrine 1:200,000 (as epinephrine bitartrate 0.009 mg/mL) (NDC 0362-9048-02)
- Articaine HCl 4% (68 mg/1.7mL) (40 mg/mL) and epinephrine 1:100,000 (as epinephrine bitartrate 0.018 mg/mL) (NDC 0362-9049-02)

Storage and Handling

Store at controlled room temperature 25°C (77°F) with brief excursions permitted between 15° and 30°C (59°F-86°F) [see USP Controlled Room Temperature]. Protect from light. Do Not Freeze.

17 PATIENT COUNSELING INFORMATION

Loss of Sensation and Muscle Function:

Inform patients in advance of the possibility of temporary loss of sensation and muscle function following infiltration and nerve block injections [see Adverse Reactions (6.2)]. Instruct patients not to eat or drink until normal sensation returns.

Methemoglobinemia:

Inform patients that use of local anesthetics may cause methemoglobinemia, a serious condition that must be treated promptly. Advise patients or caregivers to seek immediate medical attention if they or someone in their care experience the following signs or symptoms: pale, gray, or blue colored skin (cyanosis); headache; rapid heart rate; shortness of breath; lightheadedness; or fatigue.

Manufactured for SEPTODONT Inc.
205 Granite Run Dr., Suite 150, Lancaster, PA, USA 17601
Manufactured by: NOVOCOL®
Novocol Pharmaceutical of Canada Inc.
25 Wolseley Court, Cambridge, Ontario, Canada N1R 6X3

Rev 10/2023 (2552-7)

PRINCIPAL DISPLAY PANEL - 1.7 mL Cartridge Carton

FOR INFILTRATION AND NERVE BLOCK ANESTHESIA. NDC 0362-9049-02

Septocaine® (articaine HCl and epinephrine) Injection

Articaine Hydrochloride 4% (68 mg/1.7mL) (40 mg/mL) and Epinephrine 1:100,000
(Articaine Hydrochloride and Epinephrine Injection, USP)

Intraoral Submucosal Injection

Contains sodium metabisulfite.
See warnings section of insert for details.

50 single-dose cartridges: 1.7 mL each

Store at 25°C (77°F)
DO NOT PERMIT TO FREEZE

Manufactured for:
SEPTODONT, Inc.
205 Granite Run Dr., Suite 150,
Lancaster, PA, USA 17601

Manufactured by:
NOVOCOL®
Novocol Pharmaceutical of Canada, Inc.
25 Wolseley Court, Cambridge, Ontario N1R 6X3, Canada

PRINCIPAL DISPLAY PANEL - 1.7 mL Cartridge Carton

FOR INFILTRATION AND NERVE BLOCK ANESTHESIA. NDC 0362-9048-02

Septocaine® (articaine HCl and epinephrine) Injection

Articaine Hydrochloride 4% (68 mg/1.7mL) (40 mg/mL) and Epinephrine 1:200,000
(Articaine Hydrochloride and Epinephrine Injection, USP)

Intraoral Submucosal Injection

Contains sodium metabisulfite.
See warnings section of insert for details.

50 single-dose cartridges: 1.7 mL each

Store at 25°C (77°F)
DO NOT PERMIT TO FREEZE

Manufactured for:
SEPTODONT, Inc.
205 Granite Run Dr., Suite 150,
Lancaster, PA, USA 17601

Manufactured by:
NOVOCOL®
Novocol Pharmaceutical of Canada, Inc.
25 Wolseley Court, Cambridge, Ontario N1R 6X3, Canada

PRINCIPAL DISPLAY PANEL - 1.7 mL Cartridge Carton

FOR INFILTRATION AND NERVE BLOCK ANESTHESIA. NDC 0362-9049-02

Septocaine® (articaine HCl and epinephrine) Injection
Articaine Hydrochloride 4% (68 mg/1.7mL) (40 mg/mL) and Epinephrine 1:100,000
(Articaine Hydrochloride and Epinephrine Injection, USP)

Intraoral Submucosal Injection
Contains sodium metabisulfite.
See warnings section of insert for details

50 single-dose cartridges: 1.7 mL each

Store at 25°C (77°F)
DO NOT PERMIT TO FREEZE

Made by SEPTODONT
94100 Saint-Maur-des-Fossés
France